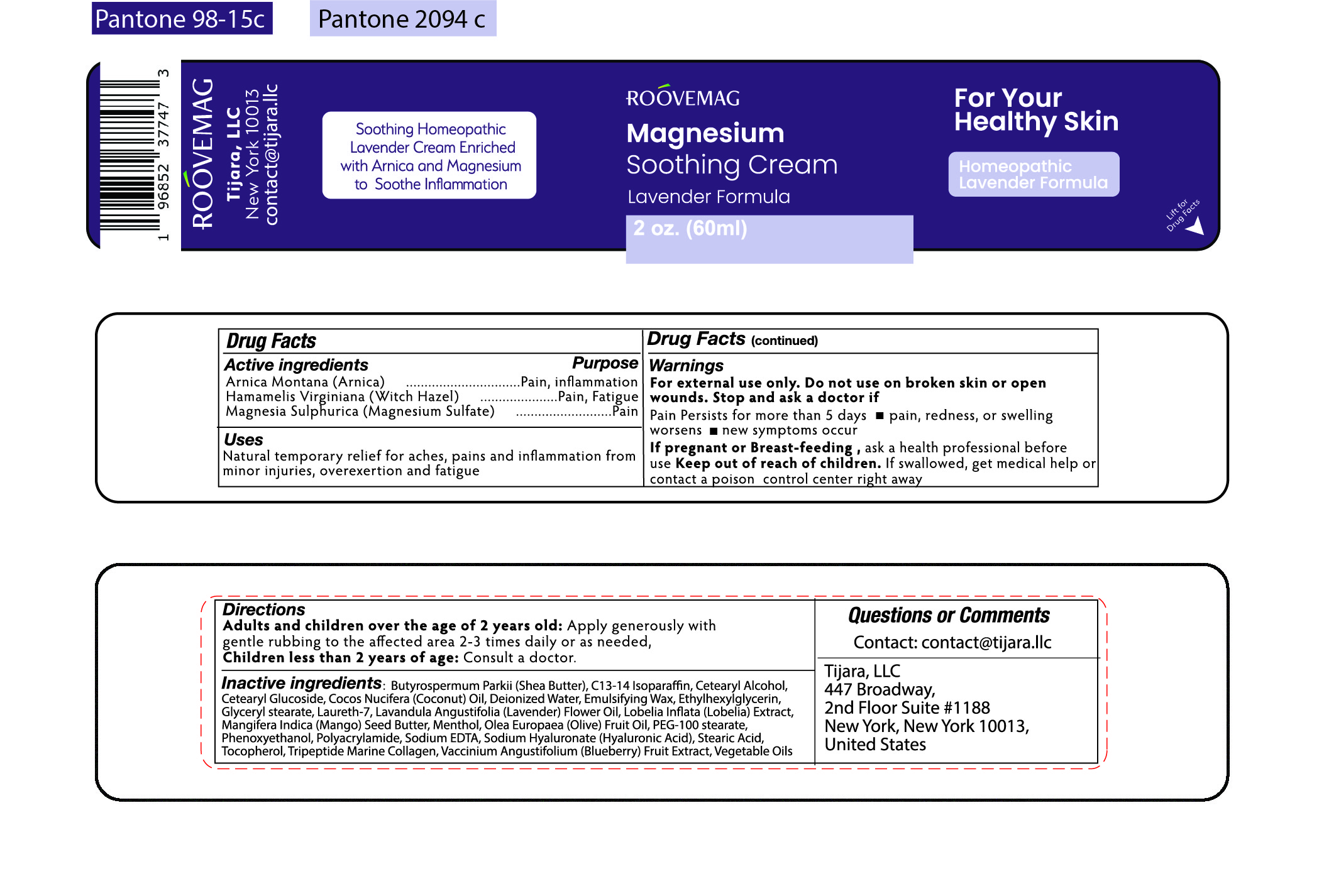 DRUG LABEL: RooveMag Magnesium Soothing Cream Lavender
NDC: 76348-404 | Form: CREAM
Manufacturer: RENU LABORATORIES, INC.
Category: homeopathic | Type: HUMAN OTC DRUG LABEL
Date: 20230324

ACTIVE INGREDIENTS: MAGNESIUM SULFATE ANHYDROUS 0.12 g/60 g; ARNICA MONTANA FLOWER 0.6 g/60 g; WITCH HAZEL 0.6 g/60 g
INACTIVE INGREDIENTS: CETEARYL GLUCOSIDE; CETOSTEARYL ALCOHOL; PHENOXYETHANOL; SODIUM ACRYLOYLDIMETHYLTAURATE-ACRYLAMIDE COPOLYMER (1:1; 90000-150000 MPA.S); MANGIFERA INDICA SEED BUTTER; LAURETH-7; OLIVE OIL; MARINE COLLAGEN, SOLUBLE; MENTHOL; HYALURONATE SODIUM; LAVENDER OIL; EDETATE SODIUM; STEARIC ACID; PEG-100 STEARATE; TOCOPHEROL; BLUEBERRY; BUTYROSPERMUM PARKII (SHEA) BUTTER UNSAPONIFIABLES; C13-14 ISOPARAFFIN; COCONUT OIL; WATER; GLYCERYL STEARATE/PEG-100 STEARATE; LOBELIA INFLATA; WHITE WAX; ETHYLHEXYLGLYCERIN

ROOVEMAG Magnesium Soothing Cream - Lavender Formula

ACTIVE INGREDIENT

Arnica Montana

Hamamelis Virginiana (Witch Hazel)

Magnesia Sulphurica (Magnesium Sulfate)

PURPOSE

Arnica . Pain, Inflammation

Witch Hazel Pain, Fatigue

Magnesim Sulfate Pain

Uses

Natural temporary relief for aches, pains and inflammation from minor injuries, overexertion and fatigue.

Warnings

For external use only. Do not use on broken skin or open wounds.

Stop and ask a doctor if

Pain persists for more than 5 days

- pain, redness, or swelling worsens
- new symptoms occur

If pregnant or Breast-feeding, ask a health professional before use

Keep out of reach of children.

If swallowed, get medical help or contact a poison control center right away

Do not use on broken skin or open wounds.

Stop and ask a doctor if

Pain persists for more than 5 days

- pain, redness, or swelling worsens
- new symptoms occur

Keep out of reach of children. If swallowed, get medical help or contact a poison control center right away.

Directions

Adults and children over the age of 2 years old: Apply generously with gentle rubbing to the affected area 2-3 times daily or as needed.

Children less than 2 years of age: Consult a doctor.

Inactive Ingredients:

Butyrospermum Parkii (Shea Butter), C13-14 Isoparaffin, Cetearyl Alcohol, Cetearyl Glucoside, Cocos Nucifera (Coconut) Oil, Deionized Water, Emulsifying Wax, Ethylhexylglycerin, Glyceryl Stearate, Laureth-7, Lavandula Angustifolia (Lavender) Flower Oil,

Lobelia Inflata (Lobelia) Extract, Mangifera Indica (Mango) Seed Butter, Menthol, Olea Europaea (Olive) Fruit Oil, PEG-100 Stearate, Phenoxyethanol, Polyacrylamide, Sodium EDTA, Sodium Hyaluronate (Hyaluronic Acid), Stearic Acid, Tocopherol, Tripeptide Marine Collagen, Vaccinium Angustifolium (Blueberr) Fruit Extract, Vegetable Oils

Questions or Comments

Contact: contact@tijara.llc

Tijara, LLC

447 Broadway

2nd Floor Suite 1188

New York, New York 10013

United States

STATEMENT OF IDENTITY

ROOVEMAG

Magnesium

Soothing Cream

Lavender Formula

PREGNANCY OR BREAST FEEDING

If pregnant or Breast feeding‚ ask a health professional before use.

ROOVEMAG MAGNESIUM SOOTHING CREAM LAVENDER LABEL